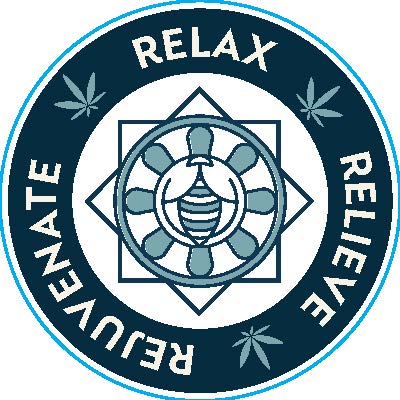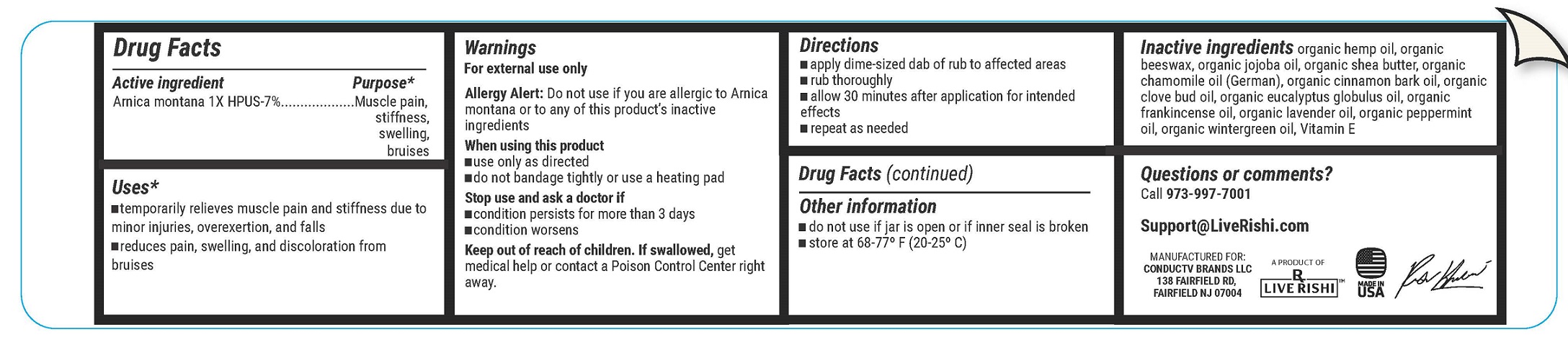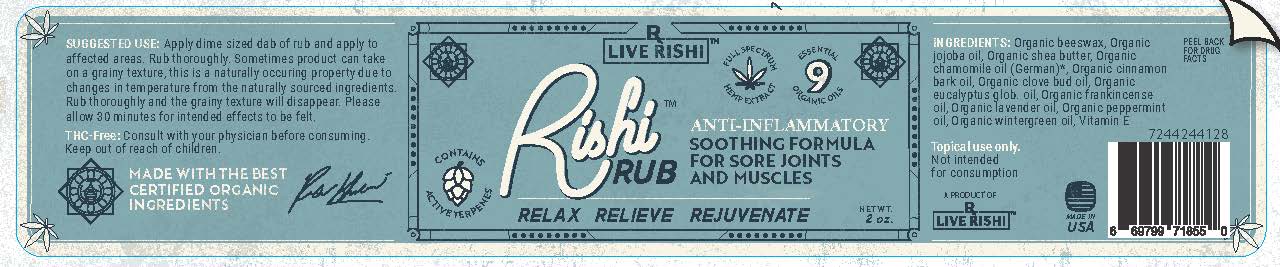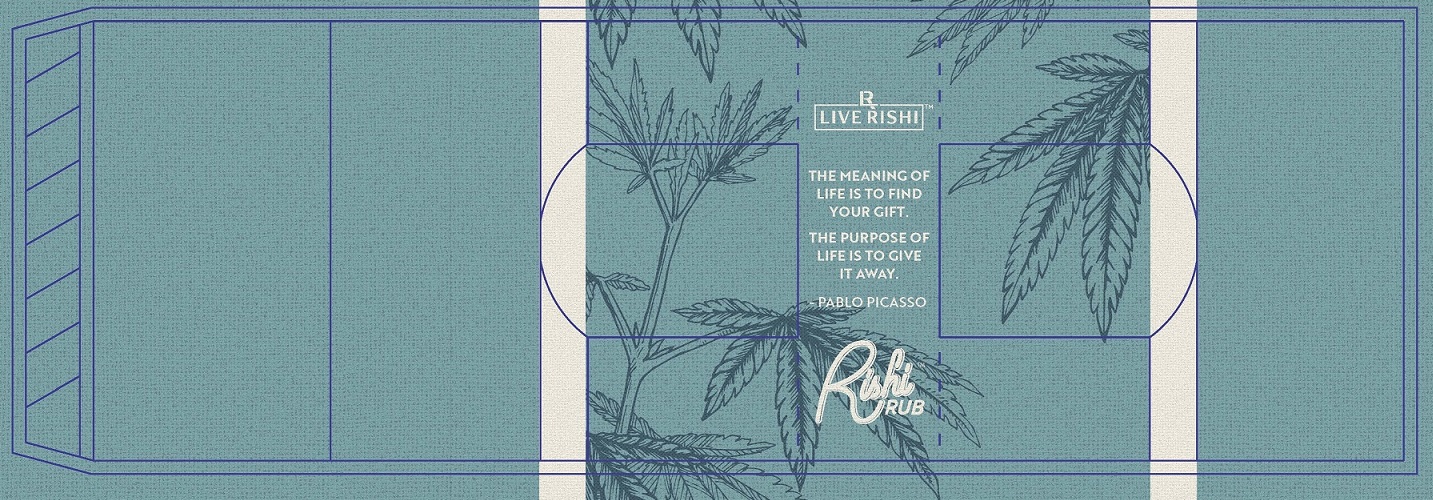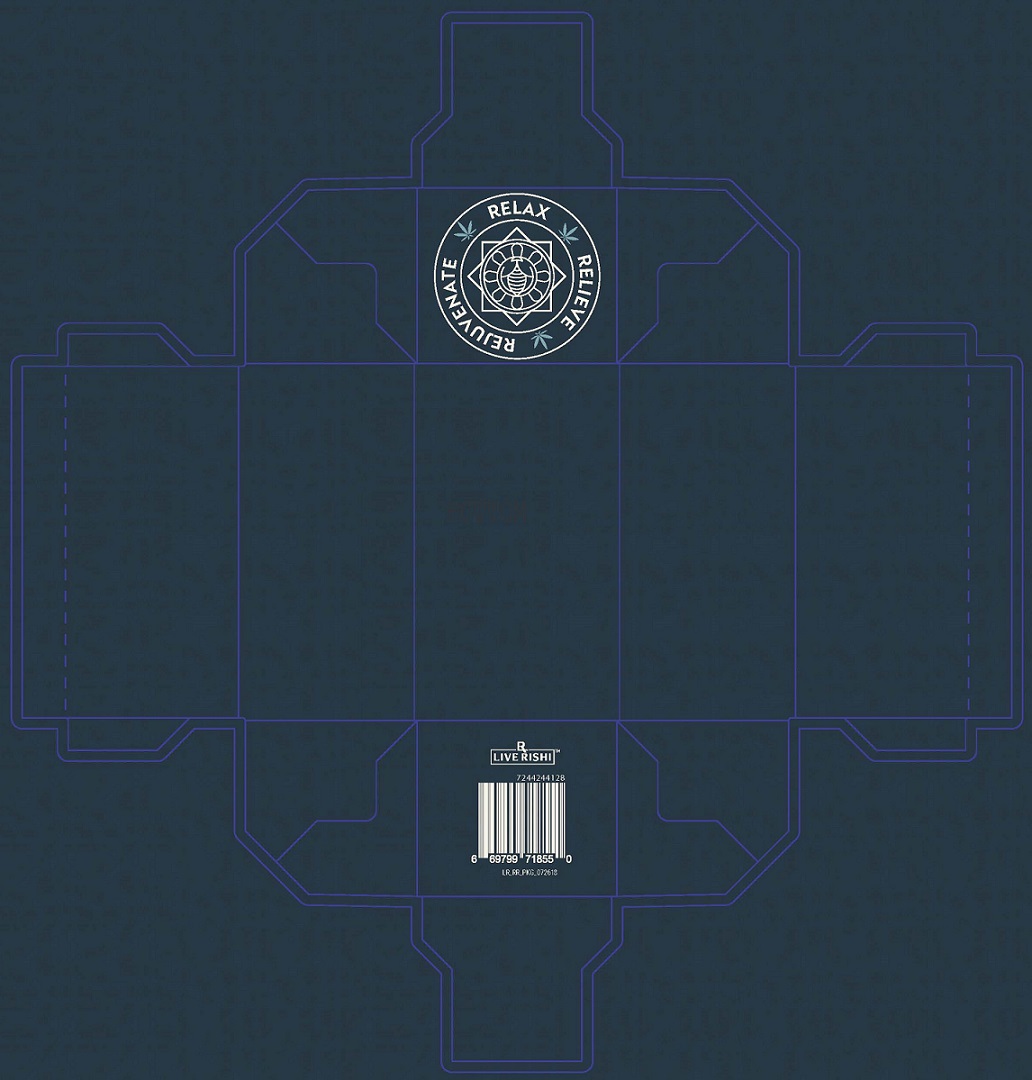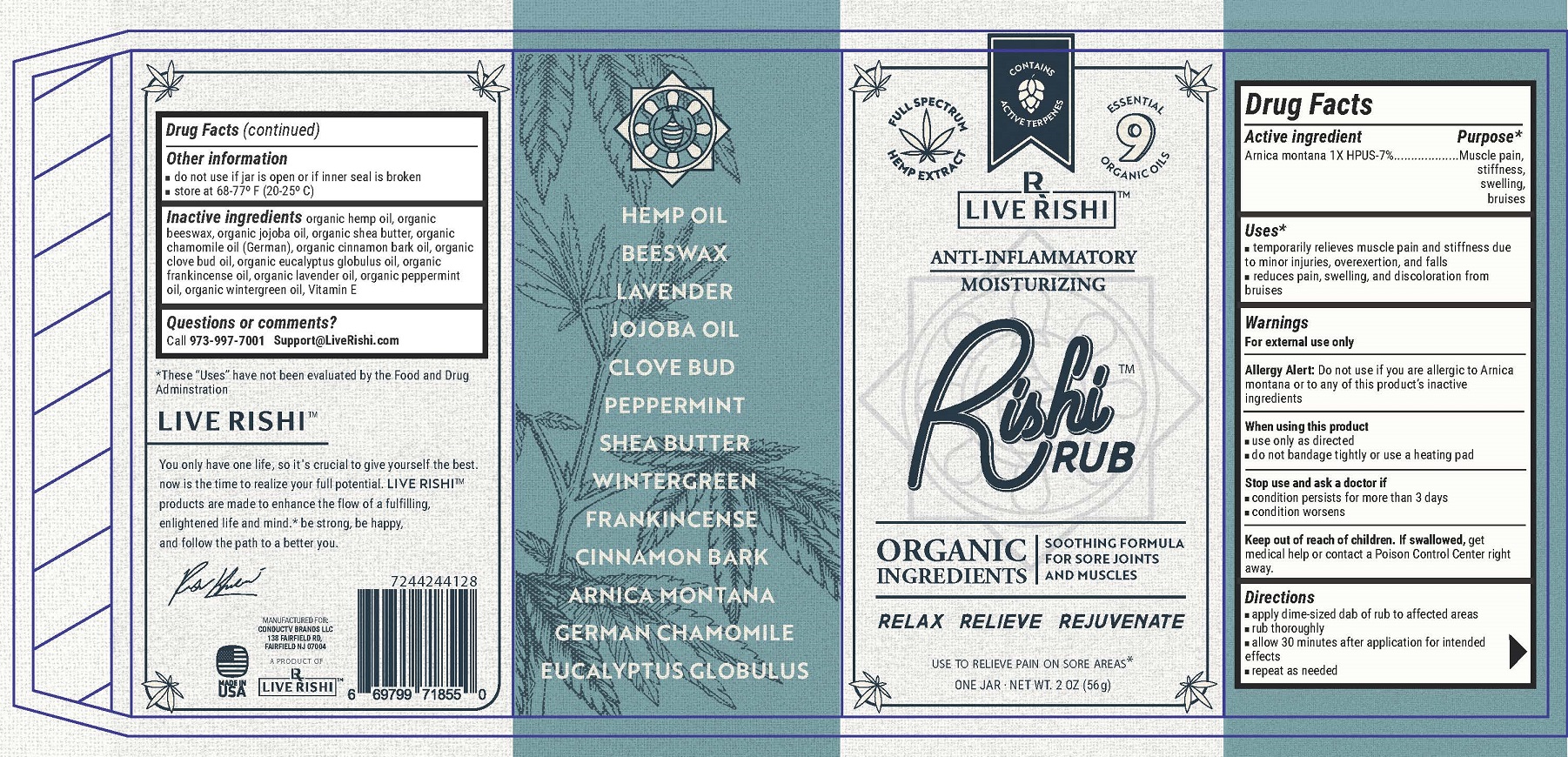 DRUG LABEL: Hemp Rub
NDC: 72442-441 | Form: CREAM
Manufacturer: ConducTV Brands LLC
Category: homeopathic | Type: HUMAN OTC DRUG LABEL
Date: 20200117

ACTIVE INGREDIENTS: ARNICA MONTANA .07 g/1 g
INACTIVE INGREDIENTS: CANNABIS SATIVA SEED OIL 1 g/1 g; YELLOW WAX 1 g/1 g; JOJOBA OIL 1 g/1 g; SHEA BUTTER 1 g/1 g; CHAMOMILE FLOWER OIL 1 g/1 g; CINNAMON BARK OIL 1 g/1 g; CLOVE OIL 1 g/1 g; EUCALYPTUS OIL 1 g/1 g; FRANKINCENSE OIL 1 g/1 g; LAVENDER OIL 1 g/1 g; PEPPERMINT OIL 1 g/1 g; METHYL SALICYLATE 1 g/1 g; .ALPHA.-TOCOPHEROL 1 g/1 g

Hemp Rub

Hemp Rub

Contains Active Terpenes

Full Spectrum Hemp Extract

9 Essential Organic Oils

Live Rishi

Anti-Inflammatory

Moisturizing

Hemp Rub

Organic Ingredients

Soothing Formula for Sore Joints and Muscles

Relax Relieve Rejuvenate

Use to Relieve Pain on Sore Areas*

One Jar - NET WT. 2 OZ (56 g)

Active Ingredient

Arnica montana 1X HPUS-7%

Purpose*

Muscle pain, stiffness, swelling, bruises

Uses*

- temporarily relieves muscle pain and stiffness due to minor injuries, overexertion, and falls
- reduces pain, swelling, and discoloration from bruises

Warnings

For external use only

Allergy Alert

Do not use if you are allergic to Arnica montana or to any of this product's inactive ingredients

When using this product

- use only as directed
- do not bandage tightly or use a heating pad

Stop use and ask a doctor if

- condition persists for more than 3 days
- condition worsens

Keep out of reach of children.

If swallowed, get medical help or contact a Poison Control Center right away.

Directions

- apply dime-sized dab of rub to affected areas
- rub thoroughly
- allow 30 minutes after application for intended effects
- repeat as needed

Other information

- do not use if jar is open or if inner seal is broken
- store at 68-77° F (20-25° C)

Inactive Ingredients

organic hemp oil, organic beeswax, organic jojoba oil, organic shea butter, organic chamomile oil (German), organic cinnamon bark oil, organic clove bud oil, organic eucalyptus globulus oil, organic frankincense oil, organic lavender oil, organic peppermint oil, organic wintergreen oil, Vitamin E

Questions or comments?

Call 973-997-7001 Support@LiveRishi.com

LIVE RISHI™

You only have one life, so it's crucial to give yourself the best. now is the time to realize your full potential. LIVE RISHI™ products are made to enhance the flow of a fulfilling, enlighted life and mind.* be strong, be happy, and follow the path to a better you.

Manufactured For:

ConducTV Brands LLC

138 Fairfield Rd,

Fairfield NJ 07004

Package Labels

Outside Box

Outside Box Top and Bottom Panels

Inside Box

Jar Label Page 1

Jar Label Page 2

Top of Jar Label